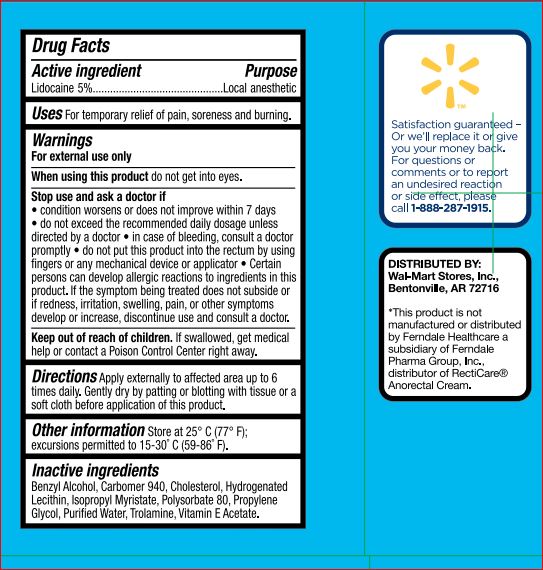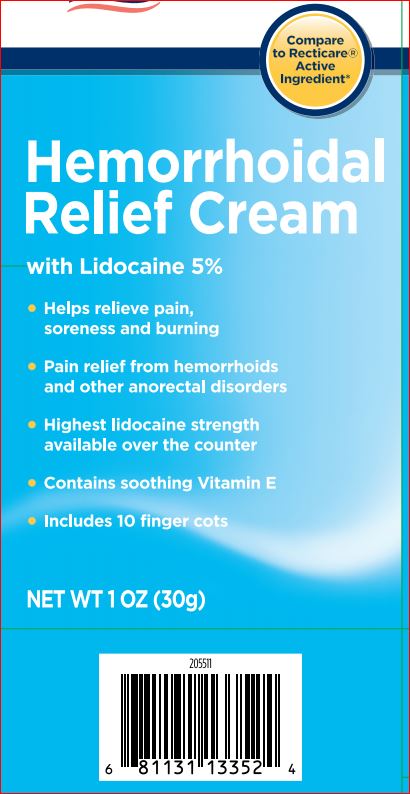 DRUG LABEL: Anorectal

NDC: 49035-655 | Form: CREAM
Manufacturer: Walmart
Category: otc | Type: HUMAN OTC DRUG LABEL
Date: 20171229

ACTIVE INGREDIENTS: LIDOCAINE 5 g/100 mL
INACTIVE INGREDIENTS: BENZYL ALCOHOL; CHOLESTEROL; HYDROGENATED SOYBEAN LECITHIN; ISOPROPYL MYRISTATE; POLYSORBATE 80; PROPYLENE GLYCOL; WATER; TROLAMINE; .ALPHA.-TOCOPHEROL ACETATE

Drug Facts FR#44-61PQ

Active ingredient Purpose

Lidocaine 5%......................................Local anesthetic

INDICATIONS AND USAGE

Uses For temporary relief of pain, soreness and burning.

Warnings For external use only

When using this product do not get into eyes.
Stop use and ask a doctor if • condition worsens or does
not improve within 7 days • do not exceed the
recommended daily dosage unless directed by a doctor
• in case of bleeding, consult a doctor promptly • do not
put this product into the rectum by using fingers or any
mechanical device or applicator

Keep out of reach of children. If swallowed, get medical
help or contact a Poison Control Center right away.

DOSAGE AND ADMINISTRATION

Directions Apply externally to affected area up to 6
times daily.

Other information Store at 25° C (77° F);
excursions permitted to 15-30˚ C (59-86˚ F).

Inactive ingredients
Benzyl Alcohol, Carbomer 940, Cholesterol, Hydrogenated Lecithin, Isopropyl Myristate, Polysorbate 80, Propylene Glycol, Purified Water, Trolamine, Vitamin E Acetate.